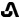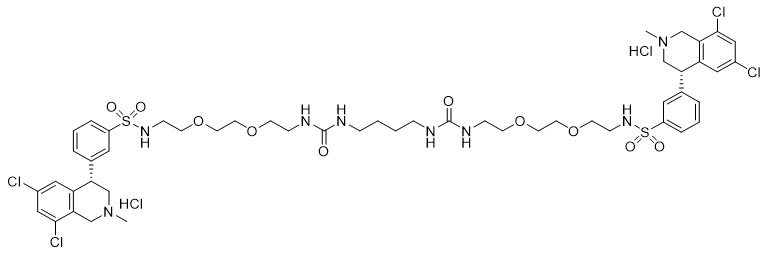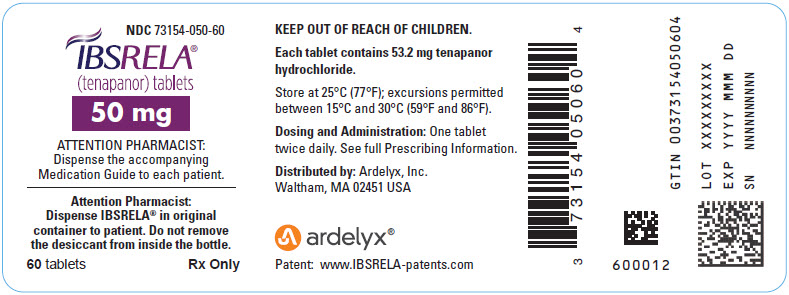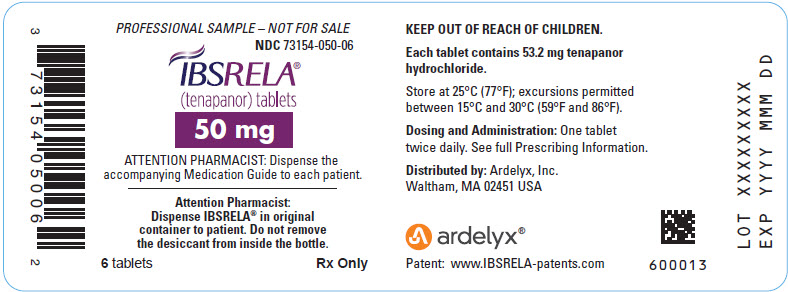 DRUG LABEL: IBSRELA
NDC: 73154-050 | Form: TABLET
Manufacturer: Ardelyx, Inc.
Category: prescription | Type: HUMAN PRESCRIPTION DRUG LABEL
Date: 20250528

ACTIVE INGREDIENTS: TENAPANOR HYDROCHLORIDE 53.2 mg/1 1

HIGHLIGHTS OF PRESCRIBING INFORMATION

These highlights do not include all the information needed to use IBSRELA® safely and effectively. See full prescribing information for IBSRELA.
IBSRELA (tenapanor) tablets, for oral use
Initial U.S. Approval: 2019

WARNING: RISK OF SERIOUS DEHYDRATION IN PEDIATRIC PATIENTS

See full prescribing information for complete boxed warning.

- IBSRELA is contraindicated in patients less than 6 years of age; in young juvenile rats, tenapanor caused death presumed to be due to dehydration. (4, 8.4)
- Avoid use of IBSRELA in patients 6 years to less than 12 years of age. (5.1, 8.4)
- The safety and effectiveness of IBSRELA have not been established in pediatric patients less than 18 years of age. (8.4)

1 INDICATIONS AND USAGE

IBSRELA is a sodium/hydrogen exchanger 3 (NHE3) inhibitor indicated for treatment of irritable bowel syndrome with constipation (IBS-C) in adults. (1)

2 DOSAGE AND ADMINISTRATION

- The recommended dosage in adults is 50 mg, orally twice daily. (2)
- Take immediately prior to breakfast or the first meal of the day and immediately prior to dinner. (2)

3 DOSAGE FORMS AND STRENGTHS

Tablets: 50 mg tenapanor. (3)

4 CONTRAINDICATIONS

- Pediatric patients less than 6 years of age. (4, 5.1, 8.4)
- Patients with known or suspected mechanical gastrointestinal obstruction. (4)

5 WARNINGS AND PRECAUTIONS

Diarrhea: Patients may experience severe diarrhea. If severe diarrhea occurs, suspend dosing and rehydrate patient. (5.2)

6 ADVERSE REACTIONS

Most common adverse reactions (≥2%) are diarrhea, abdominal distension, flatulence and dizziness. (6.1)

To report SUSPECTED ADVERSE REACTIONS, contact Ardelyx at 1-844-427-7352 or FDA at 1-800-FDA-1088 or www.fda.gov/medwatch.

7 DRUG INTERACTIONS

OATP2B1 Substrates: Potential for reduced exposure of the concomitant drug (e.g., enalapril). Monitor for signs related to loss of efficacy and adjust the dosage of the concomitantly administered drug as needed. (7.1)

FULL PRESCRIBING INFORMATION

WARNING: RISK OF SERIOUS DEHYDRATION IN PEDIATRIC PATIENTS

- IBSRELA is contraindicated in patients less than 6 years of age; in nonclinical studies in young juvenile rats administration of tenapanor caused deaths presumed to be due to dehydration [see Contraindications (4), Use in Specific Populations (8.4)].
- Avoid use of IBSRELA in patients 6 years to less than 12 years of age [see Warnings and Precautions (5.1), Use in Specific Populations (8.4)].
- The safety and effectiveness of IBSRELA have not been established in patients less than 18 years of age [see Use in Specific Populations (8.4)].

1 INDICATIONS AND USAGE

IBSRELA is indicated for treatment of irritable bowel syndrome with constipation (IBS-C) in adults.

2 DOSAGE AND ADMINISTRATION

The recommended dosage of IBSRELA in adults is 50 mg orally twice daily.

Administration Instructions

- Take IBSRELA immediately prior to breakfast or the first meal of the day and immediately prior to dinner [see Clinical Pharmacology (12.2)].
- If a dose is missed, skip the missed dose and take the next dose at the regular time. Do not take 2 doses at the same time.

3 DOSAGE FORMS AND STRENGTHS

Tablets: 50 mg tenapanor supplied as an oval, white to off-white tablet debossed with "50" on one side and "5791" on the other side.

4 CONTRAINDICATIONS

IBSRELA is contraindicated in:

- Patients less than 6 years of age due to the risk of serious dehydration [see Warnings and Precautions (5.1), Use in Specific Populations (8.4)].
- Patients with known or suspected mechanical gastrointestinal obstruction.

5 WARNINGS AND PRECAUTIONS

5.1 Risk of Serious Dehydration in Pediatric Patients

IBSRELA is contraindicated in patients below 6 years of age. The safety and effectiveness of IBSRELA in patients less than 18 years of age have not been established. In young juvenile rats (less than 1 week old; approximate human age equivalent of less than 2 years of age), decreased body weight and deaths occurred, presumed to be due to dehydration, following oral administration of tenapanor. There are no data available in older juvenile rats (human age equivalent 2 years to less than 12 years).

Avoid the use of IBSRELA in patients 6 years to less than 12 years of age. Although there are no data in older juvenile rats, given the deaths in younger rats and the lack of clinical safety and efficacy data in pediatric patients, avoid the use of IBSRELA in patients 6 years to less than 12 years of age [see Contraindications (4), Warnings and Precautions (5.2), Use in Specific Populations (8.4)].

5.2 Diarrhea

Diarrhea was the most common adverse reaction in two randomized, double-blind, placebo-controlled trials of IBS-C. Severe diarrhea was reported in 2.5% of IBSRELA-treated patients [see Adverse Reactions (6.1)]. If severe diarrhea occurs, suspend dosing and rehydrate patient.

6 ADVERSE REACTIONS

6.1 Clinical Trials Experience

Because clinical trials are conducted under widely varying conditions, adverse reaction rates observed in the clinical trials of a drug cannot be directly compared with rates in the clinical trials of another drug and may not reflect the rates observed in practice.

The safety data described below reflect data from 1203 adult patients with IBS-C in two randomized, double-blind, placebo-controlled clinical trials (Trial 1 and Trial 2). Patients were randomized to receive placebo or IBSRELA 50 mg twice daily for up to 52 weeks. Demographic characteristics were comparable between treatment groups in the two trials [see Clinical Studies (14)].

Most Common Adverse Reactions

The most common adverse reactions reported in at least 2% of patients in IBSRELA-treated patients and at an incidence greater than placebo during the 26-week double-blind placebo-controlled treatment period of Trial 1 are shown in Table 1.

Table 1: Most Common Adverse Reactions [Reported in at least 2% of patients in IBSRELA-treated patients and at an incidence greater than placebo] in Patients with IBS-C in Trial 1 (26 Weeks)
Adverse Reactions | IBSRELA N=293 % | Placebo N=300 %
Diarrhea | 16 | 4
Abdominal Distension | 3 | <1
Flatulence | 3 | 1
Dizziness | 2 | <1

The adverse reaction profile was similar during the 12-week double-blind placebo-controlled treatment period of Trial 2 (610 patients: 309 IBSRELA-treated and 301 placebo-treated) with diarrhea (15% with IBSRELA vs 2% with placebo) and abdominal distension (2% with IBSRELA vs 0% with placebo) as the most common adverse reactions.

Adverse Reaction of Special Interest – Severe Diarrhea

Severe diarrhea was reported in 2.5% of IBSRELA-treated patients compared to 0.2% of placebo-treated patients during the 26 weeks of Trial 1 and the 12 weeks of Trial 2 [see Warnings and Precautions (5.2)].

Patients with Renal Impairment

In Trials 1 and 2, there were 368 patients (31%) with baseline renal impairment (defined as eGFR less than 90 mL/min/1.73m^2). In patients with renal impairment, diarrhea, including severe diarrhea, was reported in 20% (39/194) of IBSRELA-treated patients and 0.6% (1/174) of placebo-treated patients. In patients with normal renal function at baseline, diarrhea, including severe diarrhea, was reported in 13% (53/407) of IBSRELA-treated patients and 3.5% (15/426) of placebo-treated patients. No other differences in the safety profile were reported in the renally impaired subgroup. The incidence of diarrhea and severe diarrhea in IBSRELA-treated patients did not correspond to the severity of renal impairment.

Adverse Reactions Leading to Discontinuation

Discontinuations due to adverse reactions occurred in 7.6% of IBSRELA-treated patients and 0.8% of placebo-treated patients during the 26 weeks of Trial 1 and the 12 weeks of Trial 2. The most common adverse reaction leading to discontinuation was diarrhea: 6.5% of IBSRELA-treated patients compared to 0.7% of placebo-treated patients.

Less Common Adverse Reactions

Adverse reactions reported in less than 2% of IBSRELA-treated patients and at an incidence greater than placebo during the 26 weeks of Trial 1 and the 12 weeks of Trial 2 were: rectal bleeding and abnormal gastrointestinal sounds.

Hyperkalemia

In a trial of another patient population with chronic kidney disease (defined by eGFR from 25 to 70 mL/min/1.73m^2) and Type 2 diabetes mellitus, three serious adverse reactions of hyperkalemia resulting in hospitalization were reported in 3 patients (2 IBSRELA-treated patients and 1 placebo-treated patient).

6.2 Postmarketing Experience

The following adverse reactions have been identified during post approval use of IBSRELA. Because these reactions are reported voluntarily from a population of uncertain size, it is not always possible to reliably estimate their frequency or establish a causal relationship to drug exposure.

Hypersensitivity reactions: pruritis, rash, and urticaria

7 DRUG INTERACTIONS

7.1 OATP2B1 Substrates

Tenapanor is an inhibitor of intestinal uptake transporter, OATP2B1 [see Clinical Pharmacology (12.3)]. Drugs which are substrates of OATP2B1 may have reduced exposures when concomitantly taken with IBSRELA. Monitor for signs related to loss of efficacy and adjust the dosage of concomitantly administered drug as needed.

Enalapril is a substrate of OATP2B1. When enalapril was coadministered with tenapanor (30 mg twice daily for five days, a dosage 0.6 times the recommended dosage), the peak exposure (Cmax) of enalapril and its active metabolite, enalaprilat, decreased by approximately 70% and total systemic exposures (AUC) decreased by approximately 50% to 65% compared to when enalapril was administered alone [see Clinical Pharmacology (12.3)].

Monitor blood pressure and increase the dosage of enalapril, if needed, when IBSRELA is coadministered with enalapril.

8 USE IN SPECIFIC POPULATIONS

8.1 Pregnancy

Risk Summary

Tenapanor is minimally absorbed systemically, with plasma concentrations below the limit of quantification (less than 0.5 ng/mL) following oral administration [see Clinical Pharmacology (12.3)]. Therefore, maternal use is not expected to result in fetal exposure to the drug. The available data on IBSRELA exposure from a small number of pregnant women have not identified any drug associated risk for major birth defects, miscarriage, or adverse maternal or fetal outcomes. In reproduction studies with tenapanor in pregnant rats and rabbits, no adverse fetal effects were observed in rats at 0.1 times the maximum recommended human dose and in rabbits at doses up to 8.8 times the maximum recommended human dose (based on body surface area).

The estimated background risk of major birth defects and miscarriage for the indicated population is unknown. All pregnancies have a background risk of birth defect, loss, or other adverse outcomes. In the United States general population, the estimated background risk of major birth defects and miscarriage in clinically recognized pregnancies is 2% to 4% and 15% to 20%, respectively.

Data

Animal Data

In an embryofetal development study in rats, tenapanor was administered orally to pregnant rats during the period of organogenesis at dose levels of 1, 10 and 30 mg/kg/day. Tenapanor doses of 10 and 30 mg/kg/day were not tolerated by the pregnant rats and was associated with mortality and moribundity with body weight loss. The 10 and 30 mg/kg dose group animals were sacrificed early, and the fetuses were not examined for intrauterine parameters and fetal morphology. No adverse fetal effects were observed in rats at 1 mg/kg/day (approximately 0.1 times the maximum recommended human dose) and in rabbits at doses up to 45 mg/kg/day (approximately 8.8 times the maximum recommended human dose, based on body surface area).

In a pre- and post-natal developmental study in mice, tenapanor at doses up to 200 mg/kg/day (approximately 9.7 times the maximum recommended human dose, based on body surface area) had no effect on pre- and post-natal development.

8.2 Lactation

Risk Summary

Tenapanor and its major metabolite, M1, were not detected in the breast milk of lactating women (see Data). In adults, concentrations of tenapanor were below the limit of quantitation in plasma following multiple doses of IBSRELA [see Clinical Pharmacology (12.3)]. Maternal use of IBSRELA is not expected to result in exposure to tenapanor or its major metabolite in breastfed infants. There is no information on the effects of tenapanor or its major metabolite on milk production. The developmental and health benefits of breastfeeding should be considered along with the mother's clinical need for IBSRELA and any potential adverse effects on the breastfed infant from IBSRELA or from the underlying maternal condition.

Data

A clinical lactation study was conducted in seven healthy adult women who were 22 to 37 years of age. Following oral administration of IBSRELA 50 mg twice daily for 3 days, the concentrations of tenapanor and its major metabolite were below the limit of quantitation (<1 ng/mL and <1 ng/mL) in all breast milk samples collected over 24 hours post-dosing.

8.4 Pediatric Use

IBSRELA is contraindicated in patients less than 6 years of age. Avoid IBSRELA in patients 6 years to less than 12 years of age [see Contraindications (4), Warnings and Precautions (5.1)].

The safety and effectiveness of IBSRELA in patients less than 18 years of age have not been established.

In nonclinical studies, deaths occurred in young juvenile rats (less than 1 week-old-rats approximate human age equivalent of less than 2 years of age) following oral administration of tenapanor, as described below in Juvenile Animal Toxicity Data.

Juvenile Animal Toxicity Data

In a 21-day oral dose range finding toxicity study in juvenile rats, tenapanor was administered to neonatal rats (post-natal day (PND) 5) at doses of 5 and 10 mg/kg/day. Tenapanor was not tolerated in male and female pups and the study was terminated on PND 16 due to mortalities and decreased body weight (24% to 29% reduction in females at the respective dose groups and 33% reduction in males in the 10 mg/kg/day group, compared to control).

In a second dose range finding study, tenapanor doses of 0.1, 0.5, 2.5, or 5 mg/kg/day were administered to neonatal rats from PND 5 through PND 24. Treatment-related mortalities were observed at 0.5, 2.5, and 5 mg/kg/day doses. These premature deaths were observed as early as PND 8, with majority of deaths occurring between PND 15 and 25. In the 5 mg/kg/day group, mean body weights were 47% lower for males on PND 23 and 35% lower for females on PND 22 when compared to the controls. Slightly lower mean tibial lengths (5% to 11%) were noted in males and females in the 0.5, 2.5, and 5 mg/kg/day dose groups on PND 25 and correlated with the decrements in body weight noted in these groups. Lower spleen, thymus, and/or ovarian weights were noted at the 0.5, 2.5 and 5 mg/kg/day doses. Tenapanor-related gastrointestinal distension and microscopic bone findings of increased osteoclasts, eroded bone, and/or decreased bone in sternum and/or femorotibial joint were noted in males and females in the 0.5, 2.5 and 5 mg/kg/day dose groups [see Contraindications (4), Warnings and Precautions (5.1)].

8.5 Geriatric Use

Of the 1203 patients in placebo-controlled clinical trials of IBSRELA, 100 (8%) were 65 years of age and older. No overall differences in safety or effectiveness were observed between elderly and younger patients, but greater sensitivity of some older individuals cannot be ruled out.

10 OVERDOSAGE

Based on nonclinical data, overdose of IBSRELA may result in gastrointestinal adverse effects such as diarrhea as a result of exaggerated pharmacology with a risk for dehydration if diarrhea is severe or prolonged [see Warnings and Precautions (5.1)].

11 DESCRIPTION

IBSRELA (tenapanor) tablets contain tenapanor hydrochloride as an active ingredient. Tenapanor hydrochloride is a sodium/hydrogen exchanger 3 (NHE3) inhibitor for oral use. The chemical name for tenapanor hydrochloride is 12,15-Dioxa-2,7,9-triazaheptadecanamide, 17-[[[3-[(4S)-6,8-dichloro-1,2,3,4-tetrahydro-2-methyl-4-isoquinolinyl]phenyl]sulphonyl]amino]-N-[2-[2-[2-[[[3-[(4S)-6,8-dichloro-1,2,3,4-tetrahydro-2-methyl-4-isoquinolinyl]phenyl]sulphonyl]amino]ethoxy]ethoxy]ethyl]-8-oxo-, hydrochloride (1:2). Tenapanor hydrochloride has the molecular formula of C50H68Cl6N8O10S2, the molecular weight of 1218 Daltons, and the chemical structure below:

Tenapanor hydrochloride is a white to off-white to light brown hygroscopic amorphous solid. It is practically insoluble in water.

IBSRELA tablets contain 50 mg of tenapanor (equivalent to 53.2 mg of tenapanor hydrochloride). Inactive ingredients in the tablet are colloidal silicon dioxide, low-substituted hydroxypropyl cellulose, microcrystalline cellulose, propyl gallate, stearic acid, tartaric acid, and the coating agent OPADRY®, which consists of hypromellose, titanium dioxide and triacetin.

12 CLINICAL PHARMACOLOGY

12.1 Mechanism of Action

Tenapanor is a locally acting inhibitor of the sodium/hydrogen exchanger 3 (NHE3), an antiporter expressed on the apical surface of the small intestine and colon primarily responsible for the absorption of dietary sodium. In vitro and animal studies indicate its major metabolite, M1, is not active against NHE3. By inhibiting NHE3 on the apical surface of the enterocytes, tenapanor reduces absorption of sodium from the small intestine and colon, resulting in an increase in water secretion into the intestinal lumen, which accelerates intestinal transit time and results in a softer stool consistency.

Tenapanor has also been shown to reduce abdominal pain by decreasing visceral hypersensitivity and by decreasing intestinal permeability in animal models. In rat model of colonic hypersensitivity, tenapanor reduced visceral hyperalgesia and normalized colonic sensory neuronal excitability.

12.2 Pharmacodynamics

Cardiac Electrophysiology

At 3 times the mean maximum exposure of M1 at the recommended dosage, there were no clinically relevant effects on the QTc interval.

Food Effect

Administration of IBSRELA 5 to 10 minutes before a meal increased the 24-hour stool sodium excretion compared to taking IBSRELA in the fed or fasting condition [see Dosage and Administration (2)]. In clinical trials, IBSRELA was administered immediately prior to the first meal of the day and immediately prior to dinner.

12.3 Pharmacokinetics

Absorption

Tenapanor is minimally absorbed following repeated twice daily oral administration. Plasma concentrations of tenapanor were below the limit of quantitation (less than 0.5 ng/mL) in the majority of samples from healthy subjects following single and repeated oral administration of IBSRELA 50 mg twice daily. Therefore, standard pharmacokinetic parameters such as area under the curve (AUC), maximum concentration (Cmax), and half-life (t1/2) could not be determined.

Distribution

Plasma protein binding of tenapanor and its major metabolite, M1, is approximately 99% and 97%, respectively, in vitro.

Elimination

Metabolism

Tenapanor is metabolized primarily by CYP3A4/5 and low levels of its major metabolite, M1, are detected in plasma. The Cmax of M1 is approximately 13 ng/mL after single dose of IBSRELA 50 mg and 15 ng/mL at steady state following repeated dosing of IBSRELA 50 mg twice daily in healthy subjects.

Excretion

Following administration of a single 15 mg radiolabeled ^14C-tenapanor dose to healthy subjects, approximately 70% of the radioactivity was excreted in feces within 120 hours post-dose and 79% within 240 hours post-dose, mostly as the parent drug accounting for 65% of dose within 144 hours post-dose. Approximately 9% of the administered dose was recovered in urine, primarily as metabolites. M1 is excreted in urine unchanged accounting for 1.5% of dose within 144 hours post-dose.

Specific Populations

Patients with Hepatic Impairment

Following a single dose of tenapanor 100 mg in patients with moderate hepatic impairment (Child-Pugh B), plasma concentrations of tenapanor were mostly below the limit of quantitation (< 0.5 ng/mL) and the pharmacokinetic parameters for tenapanor could not be determined. The geometric mean AUC and Cmax of the major metabolite, M1, were approximately 33% and 27% lower, respectively, in patients with moderate hepatic impairment compared to those of healthy subjects. The decrease in M1 systemic exposure is not clinically relevant.

Patients with Renal Impairment

Based on a cross-study comparison, plasma concentrations of M1 in end-stage renal disease patients on hemodialysis (eGFR less than 15 mL/min/1.73m^2) was not notably different from those of healthy subjects given comparable doses of IBSRELA.

Drug Interaction Studies

CYP Metabolism Mediated Drug Interactions

Tenapanor and M1 did not inhibit CYP1A2, CYP2B6, CYP2C8, CYP2C9, CYP2C19, and CYP2D6 in vitro.

Tenapanor and M1 did not induce CYP1A2 and CYP2B6 in vitro.

No significant inhibition or induction of CYP3A4 enzyme using midazolam as a substrate was observed when IBSRELA 50 mg was administered twice a day for 13 days in healthy subjects.

Following co-administration of a single dose of IBSRELA 50 mg with repeated doses of itraconazole 200 mg, a CYP3A4 inhibitor, the mean AUC and Cmax of M1 was decreased 50% in healthy subjects. The decrease in M1 systemic exposure is not clinically relevant. Plasma concentrations of tenapanor were mostly below the limit of quantitation (less than 0.5 ng/mL) after co-administration of itraconazole.

No significant effect on CYP2C9 activity using warfarin as a substrate was observed when tenapanor 30 mg was administered twice a day (a dosage 0.6 times the recommended dosage) for 12 days in healthy subjects.

Membrane Transporter Mediated Drug Interactions

Tenapanor inhibited OATP2B1, but is not an inhibitor of P-gp, BCRP, OATP1B1, and OATP1B3. M1 did not inhibit P-gp, BCRP, OATP1B1, OATP1B3, OAT1, OAT3, OCT2, MATE1, and MATE2-K.

M1 is a substrate of P-gp. Tenapanor is not a substrate of P-gp, BCRP, OATP1B1, and OATP1B3. M1 is not a substrate of BCRP, OAT1, OAT3, OCT2, MATE1 and MATE2-K.

No significant effect on PepT1 activity using cefadroxil as a substrate was observed when IBSRELA 50 mg was administered twice a day for 12 days in healthy subjects.

No significant effect on P-gp activity using digoxin as a substrate was observed when tenapanor 30 mg was administered twice a day (a dosage 0.6 times the recommended dosage) for 12 days in healthy subjects.

Following administration of a single 20 mg dose of enalapril (OATP2B1 substrate) with tenapanor 30 mg administered twice a day (a dosage 0.6 times the recommended dosage) at steady state in healthy subjects, the mean AUC and Cmax of enalapril was decreased by 64% and 69%, respectively. The mean AUC and Cmax of enalaprilat was decreased by 52% and 68%, respectively [see Drug Interactions (7.1)].

13 NONCLINICAL TOXICOLOGY

13.1 Carcinogenesis, Mutagenesis, Impairment of Fertility

Carcinogenesis

The carcinogenic potential of tenapanor was assessed in a 6-month carcinogenicity study in Tg rasH2 mice and in a 2-year carcinogenicity study in rats.

Tenapanor was not tumorigenic at oral doses up to 100 mg/kg/day (approximately 4.5 times the recommended human dose, based on the body surface area) in male mice and 800 mg/kg/day (approximately 39 times the maximum recommended human dose, based on the body surface area) for female mice. Tenapanor was not tumorigenic in male and female rats at oral doses up to 5 mg/kg/day (approximately 0.5 times the recommended human dose, based on the body surface area). The major metabolite of tenapanor, M1, was not tumorigenic in Tg rasH2 mice at oral doses up to 165 mg/kg/day (approximately 8 times the maximum recommended human dose, based on the body surface area)

Mutagenesis

Tenapanor was not genotoxic in the in vitro bacterial reverse mutation (Ames) assays, an in vitro chromosomal aberration assay in cultured human peripheral blood lymphocytes or the in vivo micronucleus assays in mice and rats.

Impairment of Fertility

Tenapanor had no effect on fertility or reproductive function in male rats at oral doses up to 10 mg/kg/day (approximately 0.97 times the recommended human dose, based on the body surface area) and in female mice at oral doses up to 50 mg/kg/day (approximately 2.4 times the recommended human dose, based on the body surface area).

14 CLINICAL STUDIES

The efficacy of IBSRELA for the treatment of IBS-C was established in two double-blind, placebo-controlled, randomized, multicenter trials in adult patients: Trial 1 (TEN-01-302; NCT02686138) and Trial 2 (TEN-01-301; NCT02621892). The intent-to-treat (ITT) analysis population included 620 patients in Trial 1 and 606 patients in Trial 2 with mean age of 46 years (range 18 to 75 years), 80% females, 64% White and 31% Black/African American. In these clinical trials, IBSRELA was administered immediately prior to breakfast or the first meal of the day and immediately prior to dinner.

To enter the trials, all patients met Rome III criteria for IBS-C and were required to meet the following clinical criteria during the 2-week baseline run-in period:

- a mean abdominal pain score of at least 3 on a 0-to-10-point numeric rating scale where a score of 0 indicates no pain and 10 indicates very severe pain
- less than 3 complete spontaneous bowel movements (CSBMs) per week, where a CSBM is defined as a spontaneous bowel movement (SBM) that is associated with a sense of complete evacuation (an SBM is a bowel movement occurring in the absence of laxative use)
- less than or equal to 5 SBMs per week

The trial designs were identical through the first 12 weeks of treatment, and thereafter differed in that Trial 1 continued for an additional 14 weeks of treatment (26 weeks double-blind treatment), whereas Trial 2 included a 4-week randomized withdrawal (RW) period.

Efficacy of IBSRELA was assessed using responder analyses based on daily diary entries.

In both trials, the primary endpoint was the proportion of responders, where a responder was defined as a patient achieving both the stool frequency and abdominal pain intensity responder criteria in the same week for at least 6 of the first 12 weeks of treatment. The stool frequency (CSBM) and abdominal pain responder criteria assessed each week were defined as:

- CSBM responder: a patient who experienced an increase of at least 1 CSBM in weekly average from baseline.
- Abdominal pain responder: a patient who experienced at least a 30% reduction in the weekly average of abdominal pain score compared with baseline.

The responder rates for the primary endpoint and components of the primary endpoint (CSBM and abdominal pain), which were pre-specified key secondary endpoints, are shown in Table 2.

Table 2: Efficacy Responder Rates in Placebo-Controlled Trials (Trial 1 and Trial 2) in Adults with IBS-C: Responder for at least 6 of the First 12 Weeks of Treatment
Trial 1
 | IBSRELA N=293 | Placebo N=300 | Treatment Difference [95% CI [CI: Confidence Interval] ]
Responder [A responder for these trials was defined as a patient who met both the abdominal pain and CSBM weekly responder criteria for at least 6 of the first 12 weeks.] | 37% | 24% | 13% [6%, 20%]
Components of Responder Endpoint:
CSBM Responder [A CSBM responder was defined as a patient who achieved an increase in at least 1 CSBM per week, from baseline, for a least 6 of at least 12 weeks.] | 47% | 33%
Abdominal Pain Responder [An abdominal pain responder was defined as a patient who met the criteria of at least 30% reduction from baseline in weekly average of the worst daily abdominal pain, for at least 6 of the first 12 weeks.] | 50% | 38%
Trial 2
Responder Rates | IBSRELA N=307 | Placebo N=299 | Treatment Difference [95% CI]
Responder | 27% | 19% | 8% [2%, 15%]
Components of Responder Endpoint:
CSBM Responder | 34% | 29%
Abdominal Pain Responder | 44% | 33%

In Trials 1 and 2, the proportion of responders for 9 out of the first 12 weeks, including at least 3 of the last 4 weeks, was greater in IBSRELA-treated patients compared to placebo-treated patients. In addition, in Trial 1, the proportion of responders for 13 out of 26 weeks was greater in IBSRELA-treated patients compared to placebo-treated patients.

In both trials, improvements from baseline in average weekly CSBMs and abdominal pain were observed by Week 1, with improvement maintained through the end of treatment.

In IBSRELA-treated patients re-randomized to placebo in Trial 2, CSBM frequency and abdominal pain severity worsened on average over the 4-week period but remained improved compared to baseline. Patients who continued on IBSRELA maintained their response to therapy on average over the additional 4 weeks. Patients on placebo who were re-randomized to IBSRELA had an average increase in CSBM frequency and a decrease in abdominal pain.

16 HOW SUPPLIED/STORAGE AND HANDLING

IBSRELA tablets contain 50 mg tenapanor and are oval, white to off-white, debossed with "50" on one side and "5791" on the other side.

IBSRELA is supplied in a white, opaque, high-density polyethylene bottle containing 60 tablets with a silica gel canister (as the desiccant) and screw-top polypropylene child-resistant cap lined and induction-activated aluminum foil liner (NDC 73154-050-60).

Storage

Store at room temperature, between 68°F to 77°F (20°C to 25°C).

Keep in original container and protect from moisture. Keep the container of IBSRELA tightly closed and in a dry place.

Do not remove desiccant from the bottle. Do not subdivide or repackage.

17 PATIENT COUNSELING INFORMATION

Advise the patients to read the FDA-approved patient labeling (Medication Guide).

Diarrhea

Instruct patients to stop IBSRELA and contact their healthcare provider if they experience severe diarrhea [see Warnings and Precautions (5.2)].

Accidental Ingestion

Accidental ingestion of IBSRELA in children, especially children less than 6 years of age, may result in severe diarrhea and dehydration. Instruct patients to store IBSRELA securely and out of reach of children [see Contraindications (4), Warnings and Precautions (5.1)].

Administration and Handling Instructions

Instruct Patients:

- To take IBSRELA immediately prior to breakfast or the first meal of the day and immediately before dinner [see Dosage and Administration (2)].
- If a dose is missed, skip the missed dose and take the next dose at the regular time. Do not take 2 doses at the same time [see Dosage and Administration (2)].
- To keep IBSRELA in a dry place. Protect from moisture. Keep in the original bottle. Do not remove desiccant from the bottle. Do not subdivide or repackage. Keep bottles tightly closed [see How Supplied/Storage and Handling (16)].

Manufactured for and distributed by Ardelyx, Inc.
Waltham, MA 02451 USA

IBSRELA® is a registered trademark of Ardelyx, Inc.

Patent: www.IBSRELA-patents.com

Medication Guide
IBSRELA® (ibs rel`a)
(tenapanor)
tablets, for oral use

What is the most important information I should know about IBSRELA?

- Do not give IBSRELA to children who are less than 6 years of age. It may harm them.
- You should not give IBSRELA to children 6 years to less than 18 years of age. It may harm them.

IBSRELA can cause severe diarrhea and your child could get severe dehydration (loss of a large amount of body water and salt).
See "What are the possible side effects of IBSRELA?" for more information about side effects.

What is IBSRELA?
IBSRELA is a prescription medicine used in adults to treat:

- Irritable bowel syndrome with constipation (IBS-C).

It is not known if IBSRELA is safe and effective in children less than 18 years of age.

Who should not take IBSRELA?

- Do not give IBSRELA to children who are less than 6 years of age. IBSRELA can cause severe diarrhea and your child could get severe dehydration (loss of a large amount of body water and salt).
- Do not take IBSRELA if a doctor has told you that you have a bowel blockage (intestinal obstruction).

Before you take IBSRELA, tell your doctor about all your medical conditions, including if you:

- are pregnant or plan to become pregnant. It is not known if IBSRELA will harm your unborn baby.
- are breastfeeding or plan to breastfeed, although IBSRELA is not expected to pass into your breast milk and to harm your baby. Talk with your doctor about the best way to feed your baby if you take IBSRELA.

Tell your doctor about all the medicines you take, including prescription and over-the-counter medicines, vitamins and herbal supplements.

How should I take IBSRELA?

- Take IBSRELA exactly as your doctor tells you to take it.
- Take 1 IBSRELA tablet by mouth, 2 times each day.
- Take IBSRELA immediately before breakfast or the first meal of the day and immediately before dinner.
- If a dose is missed, skip the missed dose and take the next dose at the regular time. Do not take 2 doses at the same time.

What are the possible side effects of IBSRELA?
IBSRELA can cause serious side effects, including:

- See "What is the most important information I should know about IBSRELA?"
- Diarrhea is the most common side effect of IBSRELA, and it can sometimes be severe. Stop taking IBSRELA and call your doctor if you develop severe diarrhea.

The other most common side effects of IBSRELA include:

- swelling, or a feeling of fullness or pressure in your abdomen (distension).
- gas (flatulence).
- dizziness.

These are not all the possible side effects of IBSRELA. Call your doctor for medical advice about side effects. You may report side effects to FDA at 1-800-FDA-1088. You may also report side effects to www.fda.gov/medwatch.

How should I store IBSRELA?

- Store IBSRELA at room temperature between 68°F to 77°F (20°C to 25°C).
- Keep IBSRELA in the original container and protect from moisture. Keep the container of IBSRELA tightly closed and in a dry place.
- Do not put IBSRELA in another container (repackage).
- The IBSRELA bottle contains a desiccant canister to help keep your medicine dry (protect it from moisture). Do not remove the desiccant from the bottle.

Keep IBSRELA and all medicines out of the reach of children.

General information about the safe and effective use of IBSRELA.
Medicines are sometimes prescribed for purposes other than those listed in a Medication Guide. Do not use IBSRELA for a condition for which it was not prescribed. Do not give IBSRELA to other people, even if they have the same symptoms that you have. It may harm them. You can ask your healthcare provider or pharmacist for information about IBSRELA that is written for health professionals.

What are the ingredients in IBSRELA?
Active ingredient: tenapanor hydrochloride
Inactive ingredients: colloidal silicon dioxide, hypromellose, low-substituted hydroxypropyl cellulose, microcrystalline cellulose, propyl gallate, stearic acid, tartaric acid, titanium dioxide, and triacetin.
Manufactured for and distributed by Ardelyx, Inc. Waltham, MA 02451 USA
IBSRELA® is a registered trademark of Ardelyx, Inc.
Patent: www.IBSRELA-patents.com
For more information, go to www.ardelyx.com or call 1-844-427-7352

This Medication Guide has been approved by the U.S. Food and Drug Administration.

Revised: May 2025

PRINCIPAL DISPLAY PANEL - 50 mg Tablet Bottle Label - 050-60

NDC 73154-050-60

IBSRELA®
(tenapanor) tablets

50 mg

ATTENTION PHARMACIST:
Dispense the accompanying
Medication Guide to each patient.

Attention Pharmacist:
Dispense IBSRELA® in original
container to patient. Do not remove
the desiccant from inside the bottle.

60 tablets
Rx Only

PRINCIPAL DISPLAY PANEL - 50 mg Tablet Bottle Label - 050-06

PROFESSIONAL SAMPLE – NOT FOR SALE
NDC 73154-050-06

IBSRELA®
(tenapanor) tablets

50 mg

ATTENTION PHARMACIST: Dispense the
accompanying Medication Guide to each patient.

Attention Pharmacist:
Dispense IBSRELA® in original
container to patient. Do not remove
the desiccant from inside the bottle.

6 tablets
Rx Only